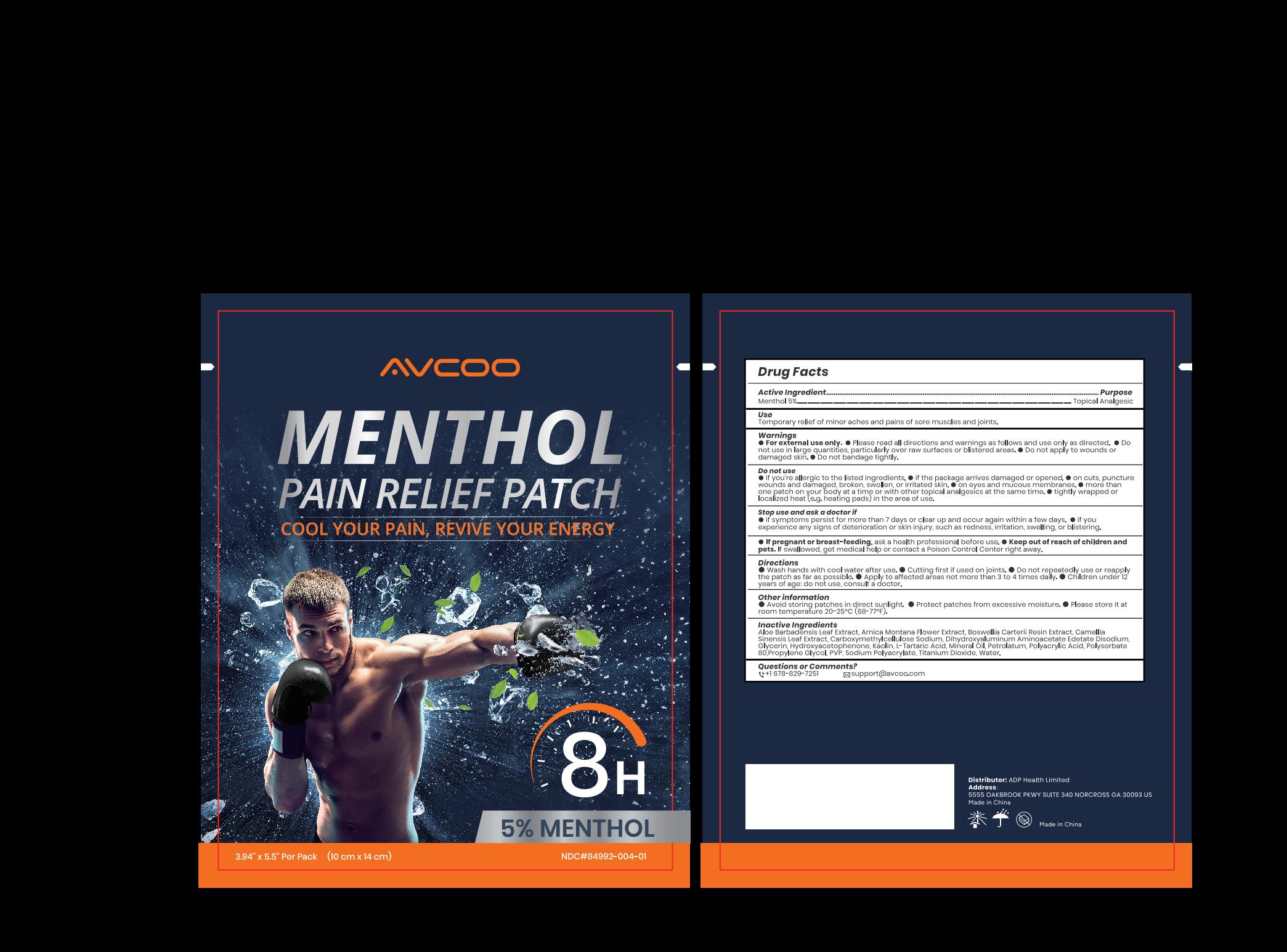 DRUG LABEL: AVCOO Menthol Pain Relief Patch
NDC: 84992-004 | Form: PATCH
Manufacturer: ADP Health Limited
Category: otc | Type: HUMAN OTC DRUG LABEL
Date: 20250313

ACTIVE INGREDIENTS: LEVOMENTHOL 500 mg/1 1
INACTIVE INGREDIENTS: PROPYLENE GLYCOL; KAOLIN; ALOE BARBADENSIS LEAF POWDER; ARNICA MONTANA FLOWER; MINERAL OIL; CARBOXYMETHYLCELLULOSE SODIUM (0.7 CARBOXYMETHYL SUBSTITUTION PER SACCHARIDE; 100-200 MPA.S AT 1%); HYDROXYACETOPHENONE; WATER; DIHYDROXYALUMINUM AMINOACETATE; PVP; POLYACRYLIC ACID (250000 MW); PETROLATUM; POLYSORBATE 80; GLYCERIN; EDETATE DISODIUM; SODIUM POLYACRYLATE (2500000 MW); TITANIUM DIOXIDE; TARTARIC ACID; FRANKINCENSE

84992-004

AVCOO Menthol Pain Relief Patch

ACTIVE INGREDIENT

Menthol 5%

PURPOSE

Topical anesthetic

INDICATIONS AND USAGE

for the temporary pain relief

WARNINGS

For external use only

DO NOT USE

If you are allergic to the listed ingredients

If you are pregnent or breast feeding

If you are under 12 years of age

On wounds, cuts, damaged/broken/irritated skin

On eyes or mucous membranes

With heating pads/devices or wrap with a bandage

With other topical analgesics

If the package arrives damaged or opened.

WHEN USING

Use only as directed

Read and follow all directions and warnings on this label

avoid contact with the eyes and mucous membranes

rare cases of serious burns have been reported with products of this type

a transient burning sensation may occur upon application but generally disappears in several days

dispose of used patch in manner that always keeps product away from children and pets. Used patches still contain the drug product that can produce serious adverse effects if a child or pet chews or ingests this patch.

STOP USE

You are experiencing pain, swelling or blistering

Redness is persent or irritation develops

Symptoms persist for more than 7 days or clear up and occur again within a few days

KEEP OUT OF REACH OF CHILDREN

If ingested, get medical help or contact a Poison Control Center right away.

DOSAGE AND ADMINISTRATION

■ Clean and dry the patch application area (no wound or hair), pull to separate the film, peel off one side of the film, apply the exposed patch to the skin, peel off the ■ Do not repeatedly use or repeatedly reapply the patch as far as possible

■ Cut first if if used on joints

■ Use in te affected area no more than 4 times daily

■ Wash hands with cool water after use

STORAGE AND HANDLING

Avoid storing patches in direct sunlight

Protect patches from excessive moisture

P lease store it at room temperature.

INACTIVE INGREDIENT

Aloe Barbadensis Leaf Extract

Arnica Montana Flower Extract

Boswellia Carterii Resin Extract

Camellia Sinensis Leaf Extract

Carboxymethylcellulose Sodium

Dihydroxyaluminum Aminoacetate

Edetate Disodium

Glycerin

Hydroxyacetophenone

Kaolin

L-Tartaric Acid

Mineral Oil

Petrolatum

Polyacrylic Acid

Polysorbate 80

Propylene Glycol

PVP

Sodium Polyacrylate

Titanium Dioxide

Water